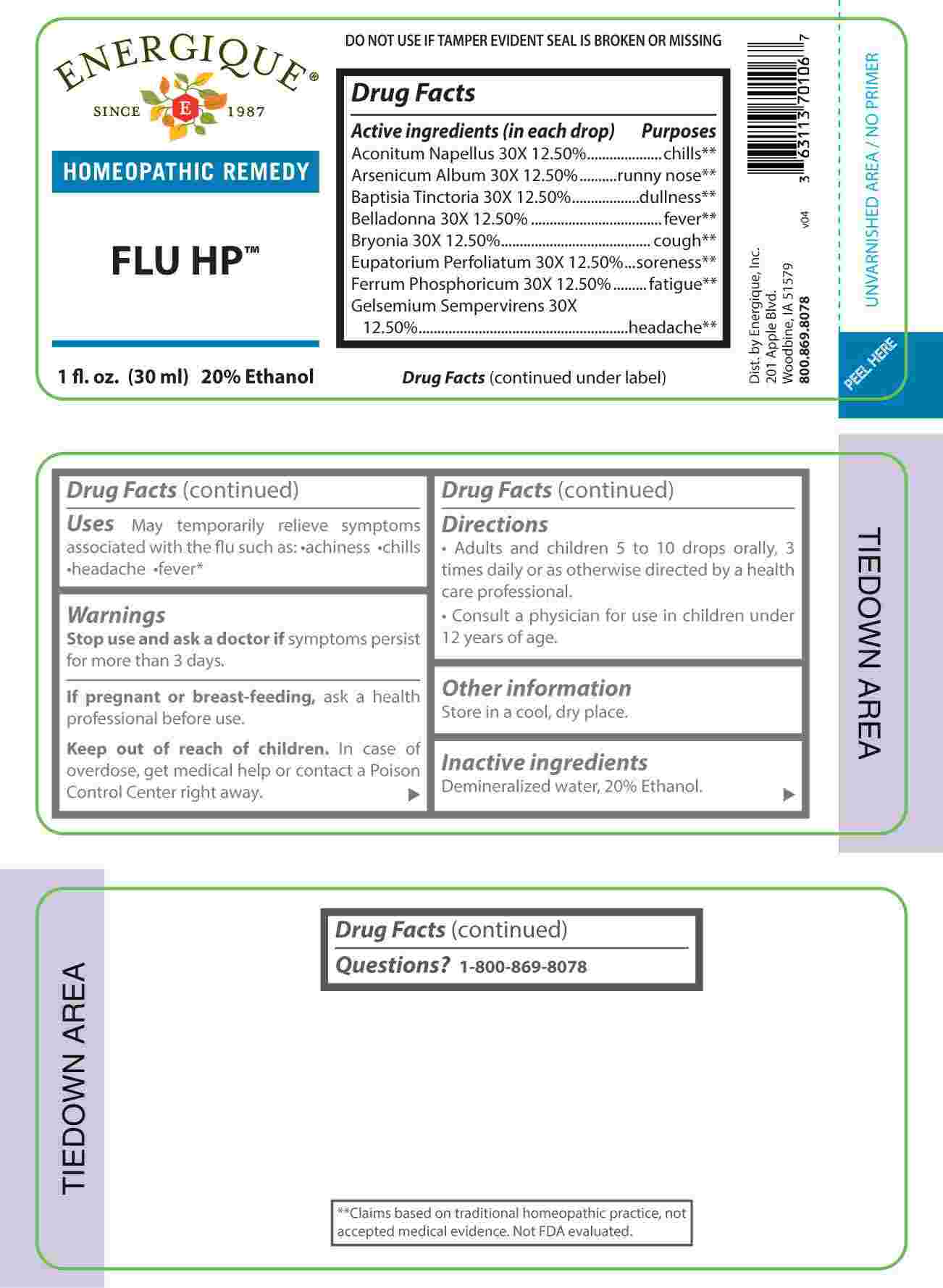 DRUG LABEL: Flu HP
NDC: 44911-0623 | Form: LIQUID
Manufacturer: Energique, Inc.
Category: homeopathic | Type: HUMAN OTC DRUG LABEL
Date: 20240924

ACTIVE INGREDIENTS: ACONITUM NAPELLUS WHOLE 30 [hp_X]/1 mL; ARSENIC TRIOXIDE 30 [hp_X]/1 mL; BAPTISIA TINCTORIA ROOT 30 [hp_X]/1 mL; ATROPA BELLADONNA 30 [hp_X]/1 mL; BRYONIA ALBA ROOT 30 [hp_X]/1 mL; EUPATORIUM PERFOLIATUM FLOWERING TOP 30 [hp_X]/1 mL; FERROSOFERRIC PHOSPHATE 30 [hp_X]/1 mL; GELSEMIUM SEMPERVIRENS ROOT 30 [hp_X]/1 mL
INACTIVE INGREDIENTS: ALCOHOL; WATER

DRUG FACTS:

ACTIVE INGREDIENTS:

(in each drop) Aconitum Napellus 30X 12.5%, Arsenicum Album 30X 12.5%, Baptisia Tinctoria 30X 12.5%, Belladonna 30X 12.5%, Bryonia 30X 12.5%, Eupatorium Perfoliatum 30X 12.5%, Ferrum Phosphoricum 30X 12.5%, Gelsemium Sempervirens 30X 12.5%.

PURPOSE:

Aconitum Napellus - chills,** Arsenicum Album – runny nose,** Baptisia Tinctoria - dullness,** Belladonna - fever,** Bryonia - cough,** Eupatorium Perfoliatum - soreness,** Ferrum Phosphoricum - fatigue,** Gelsemium Sempervirens – headache**

**Claims based on traditional homeopathic practice, not accepted medical evidence. Not FDA evaluated.

USES:

May temporarily relieve symptoms associated with the flu such as: •achiness •chills •headache •fever**

**Claims based on traditional homeopathic practice, not accepted medical evidence. Not FDA evaluated.

WARNINGS:

Stop use and ask a doctor if symptoms persist for more than 3 days.

If pregnant or breast-feeding, ask a health professional before use.

Keep out of reach of children. In case of overdose, get medical help or contact a Poison Control Center right away.

DO NOT USE IF TAMPER EVIDENT SEAL IS BROKEN OR MISSING

Store in a cool, dry place.

KEEP OUT OF REACH OF CHILDREN:

In case of overdose, get medical help or contact a Poison Control Center right away.

DIRECTIONS:

• Adults and children 5 to 10 drops orally, 3 times daily or as otherwise directed by a health professional.

• Consult a physician for use in children under 12 years of age.

INACTIVE INGREDIENTS:

Demineralized water, 20% Ethanol.

QUESTIONS:

Dist. by Energique, Inc.

201 Apple Blvd.

Woodbine, IA 51579

800.869.8078

PACKAGE LABEL DISPLAY:

ENERGIQUE

since 1987

HOMEOPATHIC REMEDY

FLU HP

1 fl. oz. (30 ml)